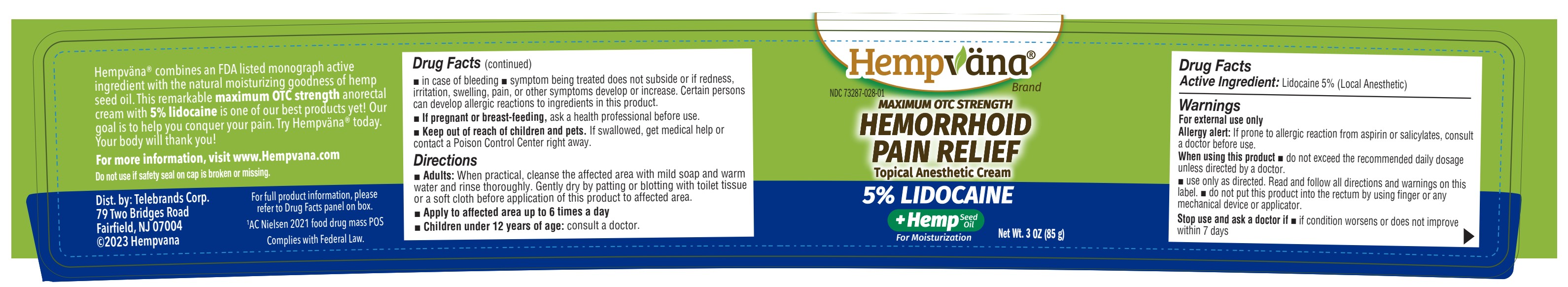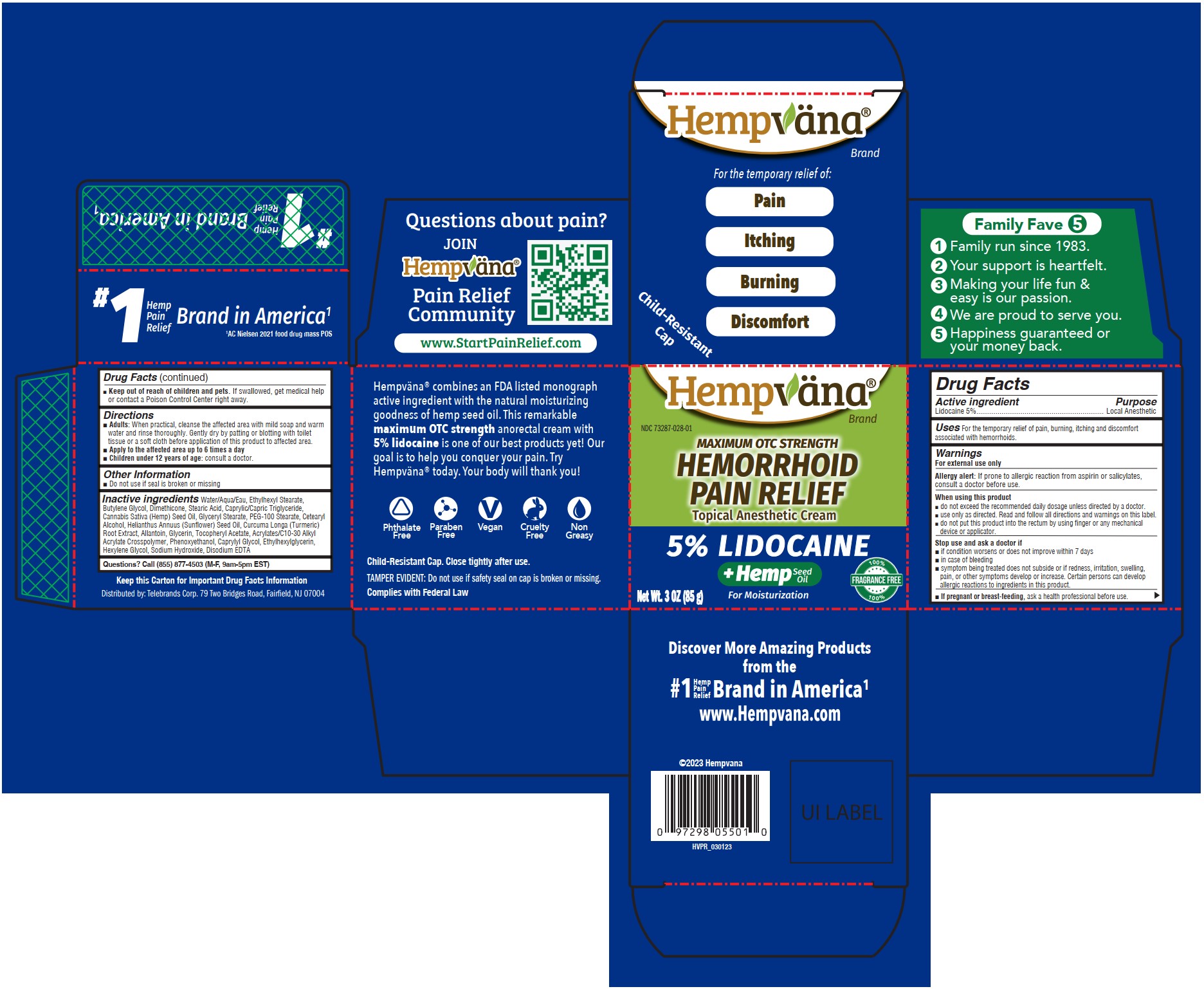 DRUG LABEL: Hemorrhoid Pain Relief
NDC: 73287-028 | Form: CREAM
Manufacturer: Telebrands Corp
Category: otc | Type: HUMAN OTC DRUG LABEL
Date: 20241120

ACTIVE INGREDIENTS: LIDOCAINE 5 g/100 g
INACTIVE INGREDIENTS: HEXYLENE GLYCOL; TURMERIC; ALLANTOIN; GLYCERIN; SUNFLOWER OIL; STEARIC ACID; CANNABIS SATIVA SEED OIL; PEG-100 STEARATE; DIMETHICONE; PHENOXYETHANOL; ACRYLATES/C10-30 ALKYL ACRYLATE CROSSPOLYMER (60000 MPA.S); ETHYLHEXYLGLYCERIN; MEDIUM-CHAIN TRIGLYCERIDES; .ALPHA.-TOCOPHEROL ACETATE; GLYCERYL MONOSTEARATE; CETOSTEARYL ALCOHOL; CAPRYLYL GLYCOL; SODIUM HYDROXIDE; EDETATE DISODIUM ANHYDROUS; ETHYLHEXYL STEARATE; BUTYLENE GLYCOL; WATER

Hemorrhoid Pain Relief

Active ingredient

Lidocaine 5%

Purpose

Lidocaine 5%................Local Anesthetic

Uses

For the temporary relief of pain, burning, itching and discomfort associated with hemorrhoids.

Warnings

For external use only

Allergy alert:If prone to allergic reaction from aspirin or salicylates, consult a doctor before use.

When using this product

- do not exceed the recommended daily dosage unless directed by a doctor.
- use only as directed. Read and follow all directions and warnings on this label.
- do not put this product into the rectum by using finger or any mechanical device or applicator.

Stop use and ask a doctor if

- if condition worsens or does not improve within 7 days
- in case of bleeding
- symptom being treated does not subside or if redness, irritation, swelling, pain, or other symptoms develop or increase. Certain persons can develop allergic reactions to ingredients in this product.

PREGNANCY OR BREAST FEEDING

If pregnant or breast-feeding,ask a health professional before use.

Keep out of reach of children and pets.If swallowed, get medical help or contact a Poison Control Center right away.

Directions

- Adults:When practical, cleanse the affected area with mild soap and warm water and rinse thoroughly. Gently dry by patting or blotting with toilet tissue or a soft cloth before application of this product to affected area.
- Apply to the affected area up to 6 times a day
- Children under 12 years of age:consult a doctor.

Other information

- Do not use if seal is broken or missing

Inactive ingredients

Water/Aqua/Eau, Ethylhexyl Stearate,Butylene Glycol, Dimethicone, Stearic Acid, Caprylic/Capric Triglyceride,Cannabis Sativa (Hemp) Seed Oil, Glyceryl Stearate, PEG-100 Stearate, CetearylAlcohol, Helianthus Annuus (Sunflower) Seed Oil, Curcuma Longa (Turmeric)Root Extract, Allantoin, Glycerin, Tocopheryl Acetate, Acrylates/C10-30 AlkylAcrylate Crosspolymer, Phenoxyethanol, Caprylyl Glycol, Ethylhexylglycerin,Hexylene Glycol, Sodium Hydroxide, Disodium EDTA

Questions?

Call (855) 877-4503 (M-F, 9am-5pm EST)

PACKAGE LABEL

Hempvana

NDC 73287-028-01

Maximum OTC Strength

Hemorrhoid Pain Relief

Topical Anesthetic Cream

5% Lidocaine

+ Hemp Seed Oil For Moisturization

Net Wt. 3oz (85g)

100% Fragrance Free